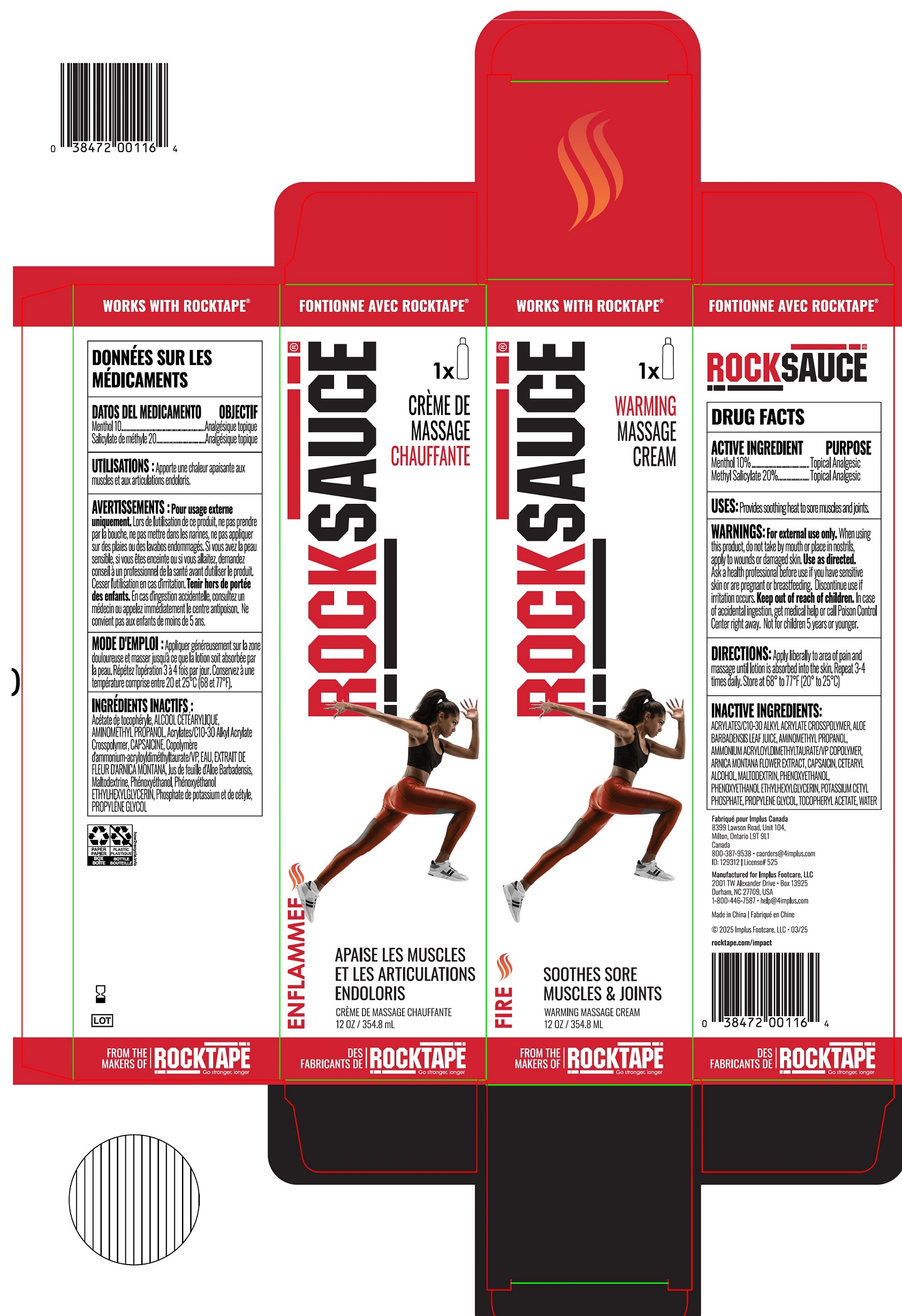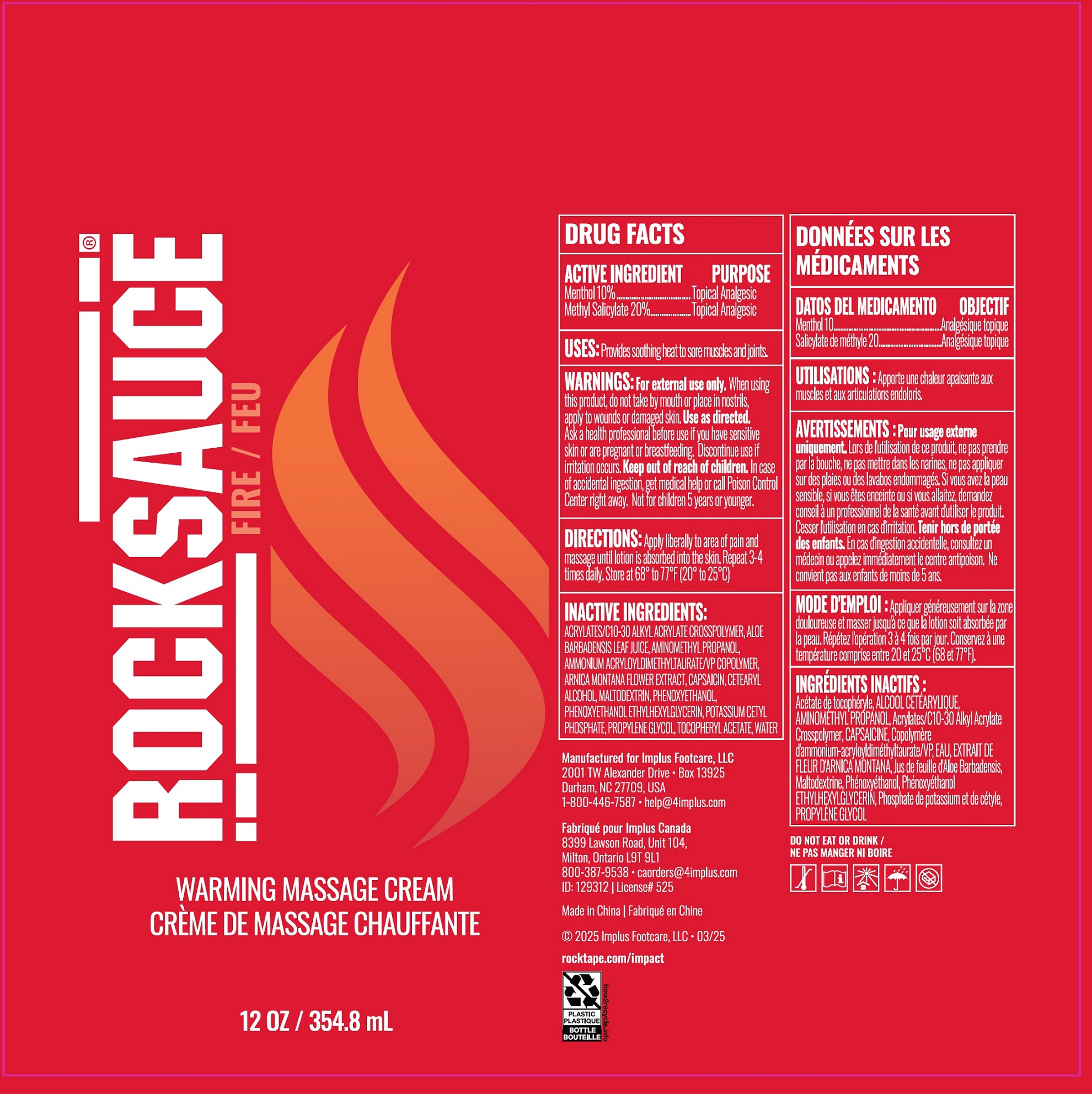 DRUG LABEL: RockSauce Cooling Massage
NDC: 81683-007 | Form: CREAM
Manufacturer: Implus Footcare, LLC
Category: otc | Type: HUMAN OTC DRUG LABEL
Date: 20260129

ACTIVE INGREDIENTS: MENTHOL 100 mg/1 mL; METHYL SALICYLATE 20 mg/1 mL
INACTIVE INGREDIENTS: ALOE VERA LEAF JUICE; AMINOMETHYLPROPANOL; AMMONIUM ACRYLOYLDIMETHYLTAURATE/VP COPOLYMER; ARNICA MONTANA FLOWER; CAPSAICIN; CETOSTEARYL ALCOHOL; MALTODEXTRIN; PHENOXYETHANOL; POTASSIUM CETYL PHOSPHATE; PROPYLENE GLYCOL; .ALPHA.-TOCOPHEROL ACETATE; WATER

RockSauce Cooling Massage Gel

ACTIVE INGREDIENT

Menthol 10%

Methyl Salicylate 20%

PURPOSE

Topical Analgesic

USES:

Provides soothing heat to sore muscles and joints.

WARNINGS:

For external use only.

When using this product,

do not take by mouth or place in nostrils, apply to wounds or damaged skin. Use as directed.

Ask a health professional before use if you have

sensitive skin or are pregnant or breastfeeding, Discontinue use if irritation occurs.

Keep out of reach of children.

In case of accidental ingestion, get medical help or call Poison Control Center right away. Not for children 5 years or younger.

DIRECTIONS:

Apply liberally to area of pain and massage until lotion is absorbed into the skin. Repeat 3-4 times daily. Store at 68º to 77ºF (20º to 25ºC)

INACTIVE INGREDIENTS:

ACRYLATES/C10-30 ALKYL ACRYLATE CROSSPOLYMER, ALOE BARBADENSIS LEAF JUICE, AMINOMETHYL PROPANOL, AMMONIUM ACRYLOYLDIMETHYLTAURATE/VP COPOLYMER, ARNICA MONTANA FLOWER EXTRACT, CAPSAICIN, CETEARYL ALCOHOL, MALTODEXTRIN, PHENOXYETHANOL, PHENOXYETHANOL ETHYLHEXYLGLYCERIN, POTASSIUM CETYL PHOSPHATE, PROPYLENE GLYCOL, TOCOPHERYL ACETATE, WATER